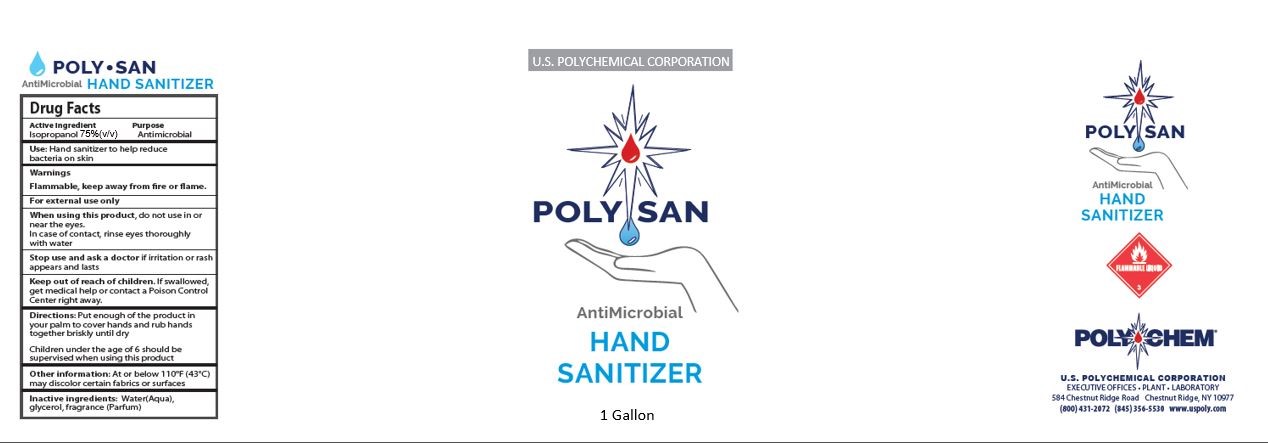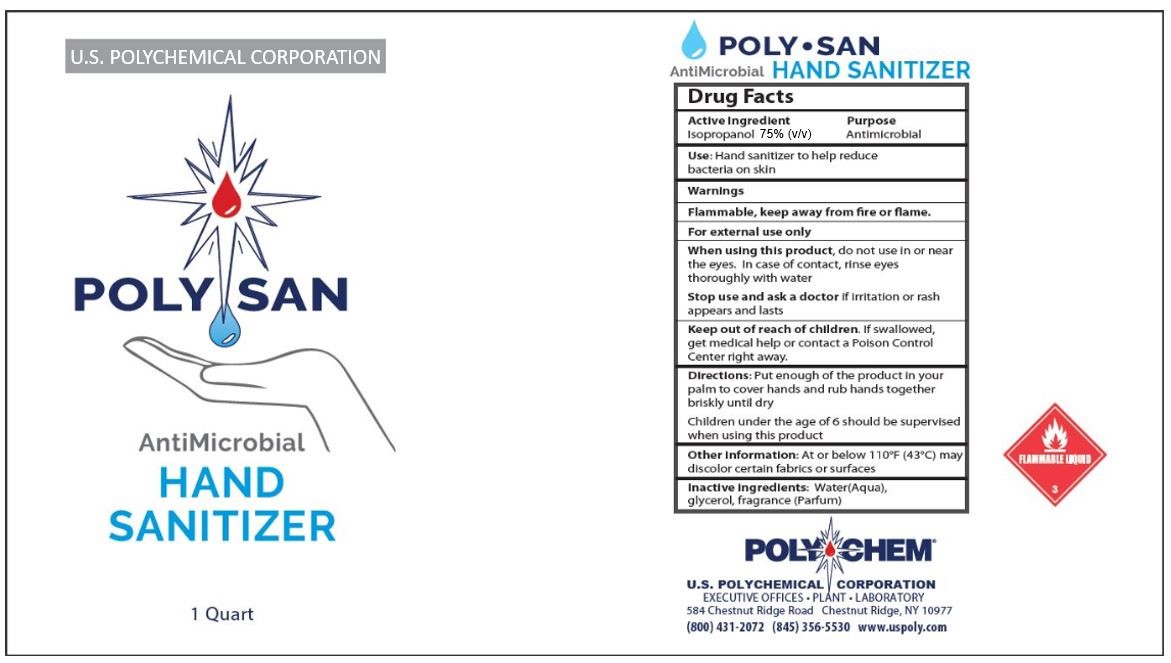 DRUG LABEL: Poly San Hand Sanitizer
NDC: 76644-0001 | Form: LIQUID
Manufacturer: US Polychemical Holding Corporation
Category: otc | Type: HUMAN OTC DRUG LABEL
Date: 20200430

ACTIVE INGREDIENTS: ISOPROPYL ALCOHOL 2.846 L/3.785 L
INACTIVE INGREDIENTS: WATER 0.86 L/3.785 L; GLYCERIN 0.076 L/3.785 L; COUMARIN 0.000001445 L/3.785 L; HEXAMETHYLINDANOPYRAN 0.00001445 L/3.785 L; TERPINEOL 0.00001445 L/3.785 L; BENZYL ACETATE 0.000007225 L/3.785 L; TERPINYL ACETATE 0.000007225 L/3.785 L; PHENYLETHYL ALCOHOL 0.00001445 L/3.785 L; CINNAMYL ALCOHOL 0.000001445 L/3.785 L; DECANAL 0.000001445 L/3.785 L; PHENYLACETALDEHYDE 0.000001445 L/3.785 L; ISOMETHYL-.ALPHA.-IONONE 0.000001445 L/3.785 L; .ALPHA.-AMYLCINNAMALDEHYDE 0.00001445 L/3.785 L; GERANIOL 0.00001445 L/3.785 L; BUTYLPHENYL METHYLPROPIONAL 0.00001445 L/3.785 L; LINALOOL, (+/-)- 0.00000289 L/3.785 L; 4-TERT-BUTYLCYCLOHEXANYL ACETATE, TRANS- 0.0000289 L/3.785 L; EUGENOL 0.000001445 L/3.785 L; DIHYDROMYRCENOL 0.000001445 L/3.785 L; LINALYL ACETATE, (+)- 0.000001445 L/3.785 L; LIMONENE, (+/-)- 0.00000578 L/3.785 L; HYDROXYISOHEXYL 3-CYCLOHEXENE CARBOXALDEHYDE 0.000001445 L/3.785 L; 3,3'-DIHYDROXYDIPROPYL ETHER 0.00007225 L/3.785 L

Poly San Liquid Hand Sanitizer
(Isopropyl Alcohol based Hand Sanitizer)

Poly San Hand Sanitizer; Purpose

Purpose: Antimicrobial

Poly San Hand Sanitizer; Active Ingredient Section

Active Ingredient: Isopropyl Alcohol.....75%(v/v)

Poly San Hand Sanitizer; Indications & Usage Section

Use: Hand sanitizer tTo help reduce the amount of bacteria on the skin.

Poly San Hand Sanitzer; Do Not Use Section

For external use only, do not use

• on children less than 2 months of age

• on an open skin wound

• in or near the eyes, ears or mouth

In case of contact, rinse eyes thoroughly with water

Poly San Hand Sanitzer; Warnings Section

Warnings: Flammable, keep away from fire or flame.

Poly San Hand Sanitizer Gel; Stop use and ask Doctor if section

Stop use and ask Doctor if irritation appears and lasts

Poly San Hand Sanitizer; Keep out of reach of children section

Keep out of reach of children: If swallowed, get medical help or contact a Poison Control Center right away.

Poly San Hand Sanitizer; Dosage & Administration Section

Directions: Put enough of the product in your palm to cover hands and rub hands together briskly until dry.

Children under the age of 6 should be supervised when using this product

Poly San Hand Sanitizer; Inactive Ingredient Section

Inactive ingredients: Water(Aqua), glycerol, Fragrance (Parfum)

Poly San Hand Sanitizer Gel; Other Safety Information

Other information: At or below 110°F (43°C) may discolor certain fabrics or surfaces.

Avoid freezing and excessive heat.

Store between 59-86°F (15-30°C).

Poly San Hand Sanitzer Drug Facts Label The following Hand sanitizer is manufactured according to the 1994 TFM for OTC antiseptic drug products that published in the Federal Register of June 17, 1994 (59 FR 31402).

Drug Facts

Active Ingredient: Isopropanol 75% (v/v) Purpose: Antimicrobial

Use: Hand sanitizer to help reduce bacteria on skin

Warnings: Flammable, keep away from fire or flame.

For external use only, do not use

• on children less than 2 months of age

• on an open skin wound

• in or near the eyes, ears or mouth

In case of contact, rinse eyes thoroughly with water

Stop use and ask a doctor if irritation or rash appears and lasts

Keep out of reach of children. If swallowed, get medical help or contact a Poison Control Center right away.

Directions: Put enough of the product in your palm to cover hands and rub hands together briskly until dry

Children under the age of 6 should be supervised when using this product

Other information: At or below 110°F (43°C) may discolor certain fabrics or surfaces.

Avoid freezing and excessive heat.

Store between 59-86°F (15-30°C).

Inactive ingredients: Water(Aqua),glycerol, fragrance (Parfum)

Poly San Hand Sanitizer Gallon Size 1.jpg

Poly San Hand Sanitizer Qt size 1.jpg